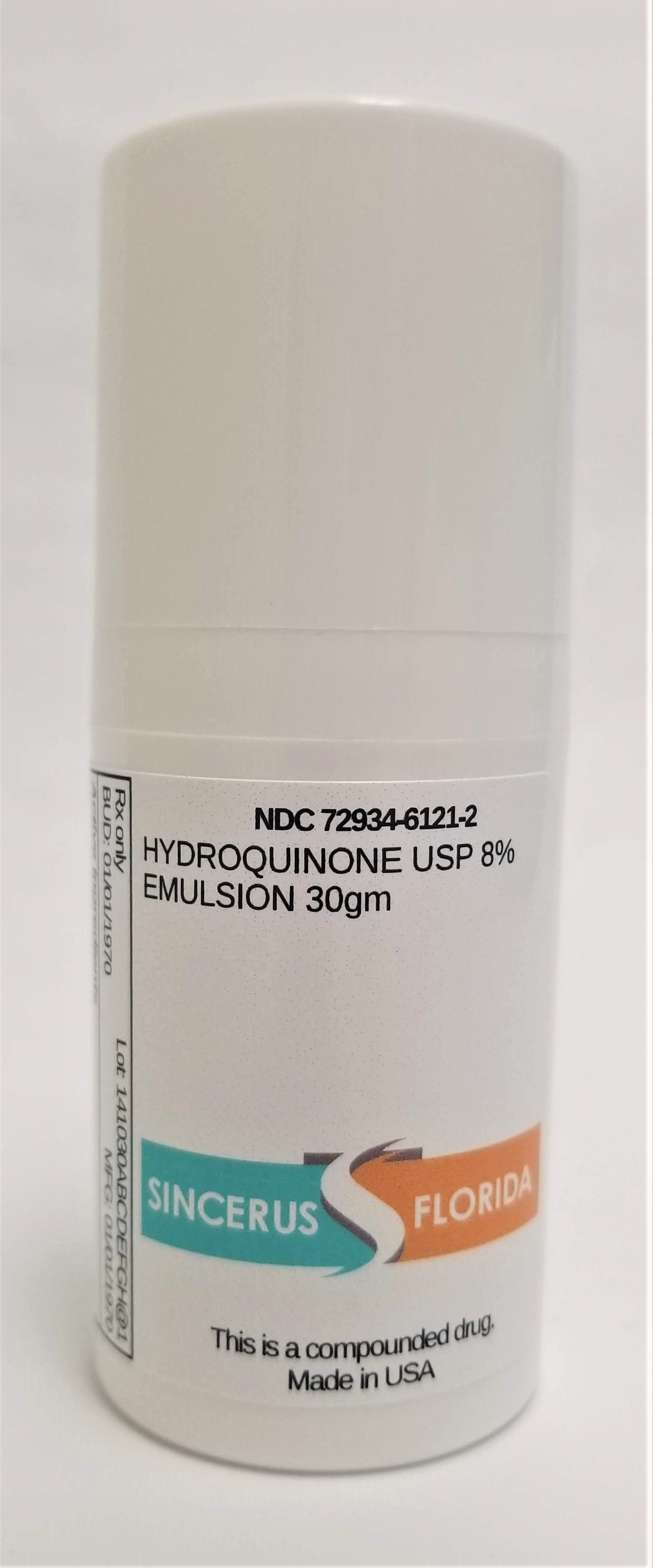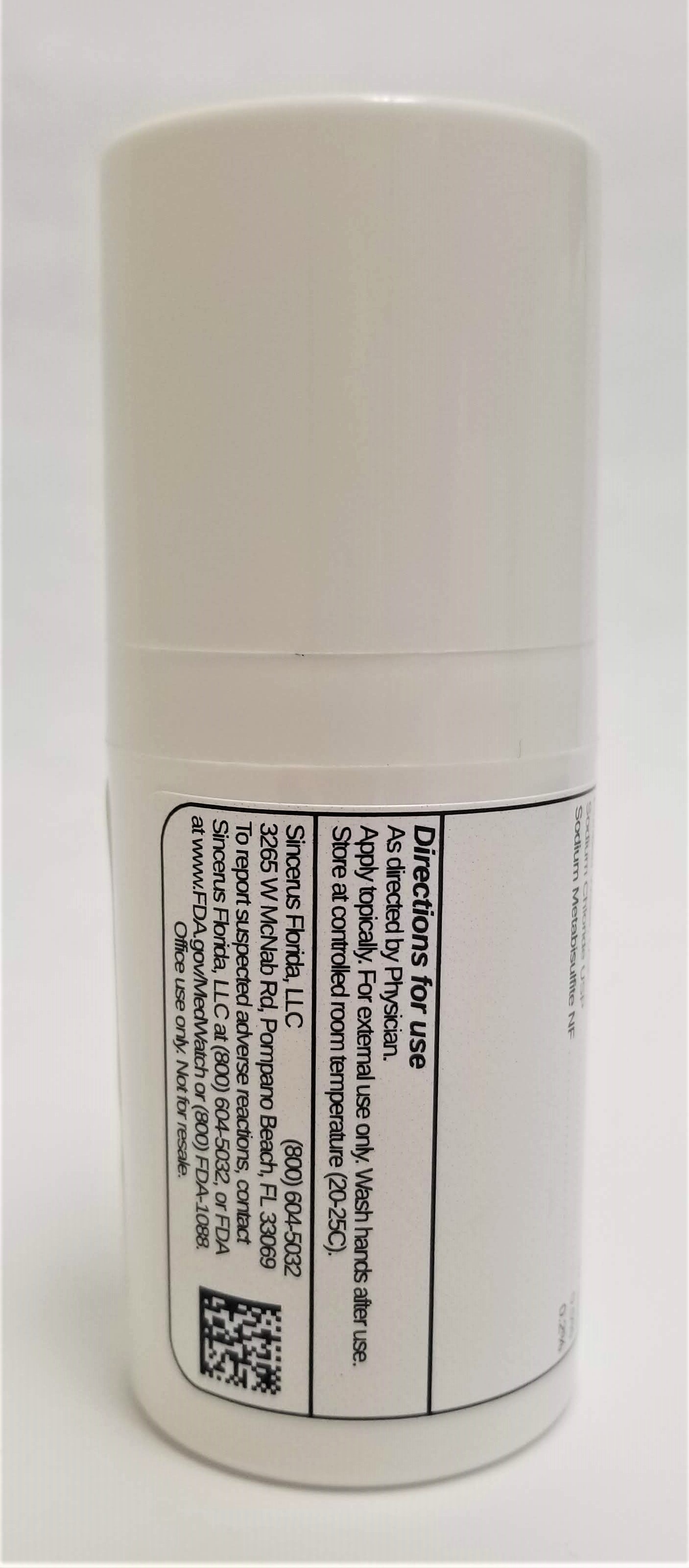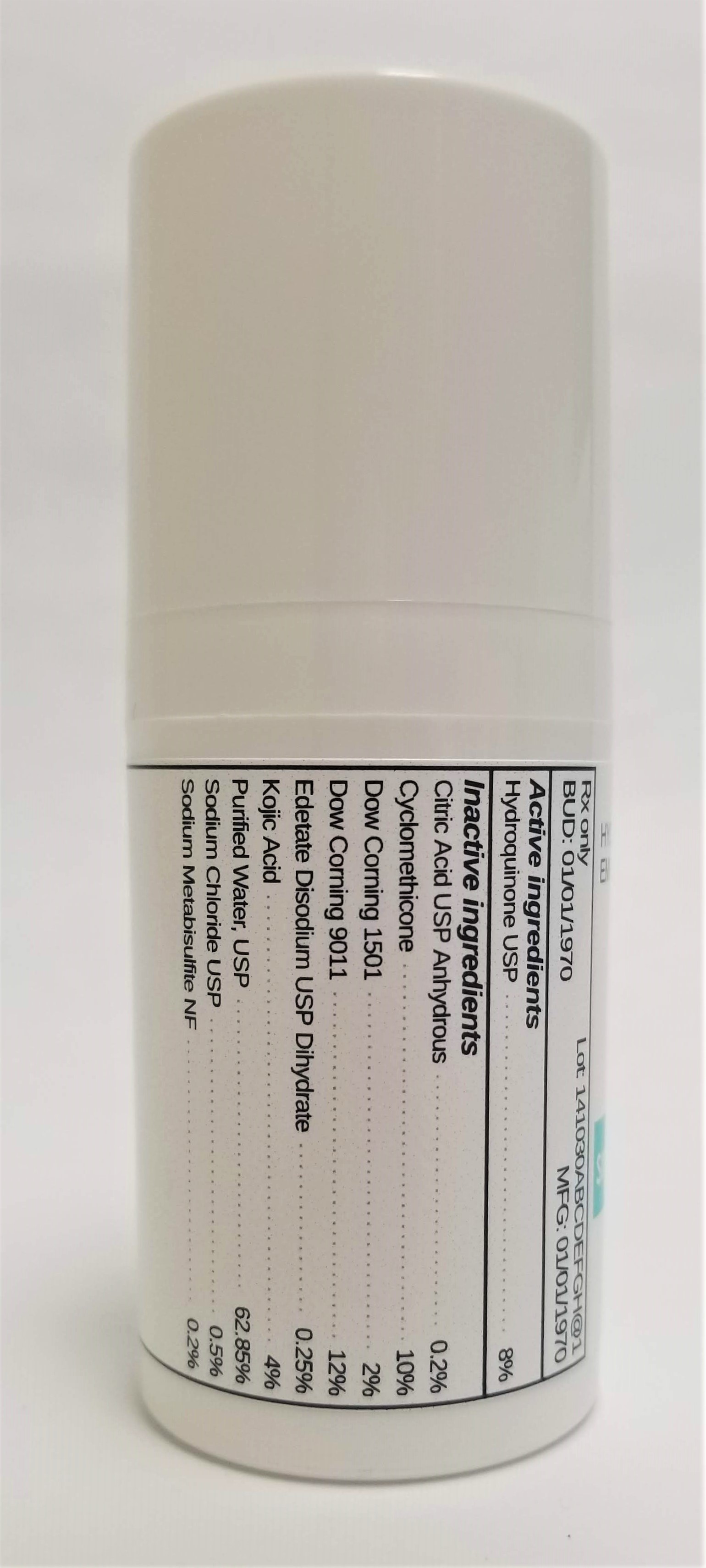 DRUG LABEL: HYDROQUINONE 8%
NDC: 72934-6121 | Form: EMULSION
Manufacturer: Sincerus Florida, LLC
Category: prescription | Type: HUMAN PRESCRIPTION DRUG LABEL
Date: 20190424

ACTIVE INGREDIENTS: HYDROQUINONE 8 g/100 g

HYDROQUINONE 8%